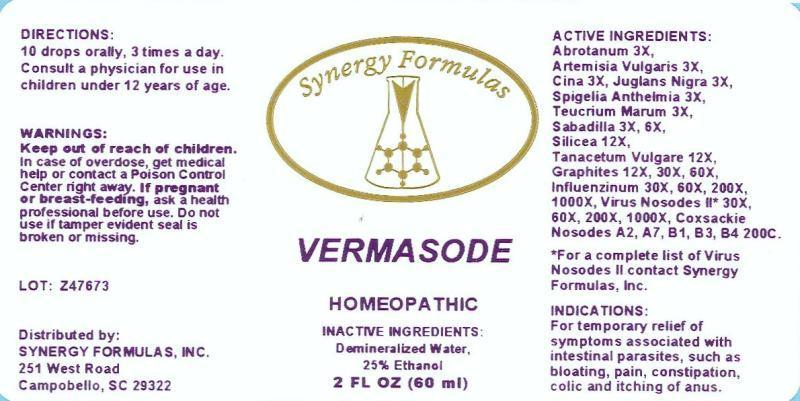 DRUG LABEL: Vermasode
NDC: 43772-0025 | Form: LIQUID
Manufacturer: Synergy Formulas, Inc.
Category: homeopathic | Type: HUMAN OTC DRUG LABEL
Date: 20150116

ACTIVE INGREDIENTS: ARTEMISIA ABROTANUM FLOWERING TOP 3 [hp_X]/1 mL; ARTEMISIA VULGARIS ROOT 3 [hp_X]/1 mL; ARTEMISIA CINA PRE-FLOWERING TOP 3 [hp_X]/1 mL; BLACK WALNUT 3 [hp_X]/1 mL; SPIGELIA ANTHELMIA 3 [hp_X]/1 mL; TEUCRIUM MARUM 3 [hp_X]/1 mL; SCHOENOCAULON OFFICINALE SEED 3 [hp_X]/1 mL; SILICON DIOXIDE 12 [hp_X]/1 mL; TANACETUM VULGARE TOP 12 [hp_X]/1 mL; GRAPHITE 12 [hp_X]/1 mL; INFLUENZA A VIRUS 30 [hp_X]/1 mL; INFLUENZA B VIRUS 30 [hp_X]/1 mL; MEASLES VIRUS 30 [hp_X]/1 mL; DIPHTHERIAL RESPIRATORY PSEUDOMEMBRANE HUMAN 30 [hp_X]/1 mL; HUMAN HERPESVIRUS 4 30 [hp_X]/1 mL; HUMAN HERPESVIRUS 3 30 [hp_X]/1 mL; POLIOVIRUS 30 [hp_X]/1 mL; HAEMOPHILUS INFLUENZAE TYPE B 30 [hp_X]/1 mL; HEPATITIS A VIRUS 30 [hp_X]/1 mL; HEPATITIS C VIRUS 30 [hp_X]/1 mL; STREPTOCOCCUS PNEUMONIAE 30 [hp_X]/1 mL; HUMAN COXSACKIEVIRUS A2 200 [hp_C]/1 mL; HUMAN COXSACKIEVIRUS A7 200 [hp_C]/1 mL; HUMAN COXSACKIEVIRUS B1 200 [hp_C]/1 mL; HUMAN COXSACKIEVIRUS B3 200 [hp_C]/1 mL; HUMAN COXSACKIEVIRUS B4 200 [hp_C]/1 mL
INACTIVE INGREDIENTS: WATER; ALCOHOL

DRUG FACTS:

ACTIVE INGREDIENTS:

Abrotanum, Artemisia Vulgaris, Cina, Juglans Nigra, Spigelia Anthelmia, Teucrium Marum 3X, Sabadilla 3X, 6X, Silicea, Tanacetum Vulgare 12X, Graphites 12X, 30X, 60X, Influenzinum 30X, 60X, 200X, 1000X, Morbillinum, Diphtherinum, Mononucleosis Virus Nosode, Epstein-Barr Virus Nosode, Herpes Zoster Nosode, Poliomyelitis Nosode, Haemophilus, Hepatitis A Nosode, Hepatitis C Nosode, Pneumococcinum 30X, 60X, 200X, 1000X, Coxsackie A2, A7, B1, B3, B4 Nosode 200C.

INDICATIONS:

For temporary relief of symptoms associated with intestinal parasites, such as bloating, pain constipation, colic and itching of anus.

WARNINGS:

Keep out of reach of children. In case of overdose, get medical help or contact a Poison Control Center right away.

If pregnant or breast-feeding, ask a health professional before use.

Do not use if tamper evident seal is broken or missing.

Keep out of reach of children. In case of overdose, get medical help or contact a Poison Control Center right away.

DIRECTIONS:

10 drops orally, 3 times a day. Consult a physician for use in children under 12 years of age.

INDICATIONS:

For temporary relief of symptoms associated with intestinal parasites, such as bloating, pain constipation, colic and itching of anus.

INACTIVE INGREDIENTS:

Demineralized Water, 25% Ethanol

QUESTIONS:

Distributed by:

SYNERGY FORMULAS, INC.

251 West Road

Campobello, SC 29322

PACKAGE LABEL DISPLAY:

Synergy Formulas

VERMASODE

HOMEOPATHIC

2 FL OZ (60 ml)